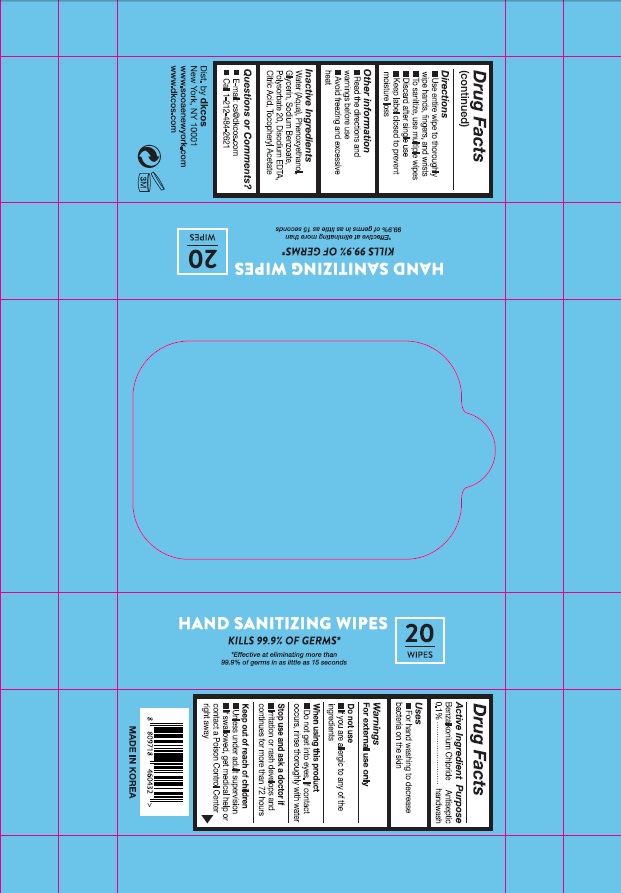 DRUG LABEL: SooAe Hand Sanitizing Wipes
NDC: 73923-0160 | Form: CLOTH
Manufacturer: FIRSTCHAM CO., LTD
Category: otc | Type: HUMAN OTC DRUG LABEL
Date: 20220114

ACTIVE INGREDIENTS: Benzalkonium Chloride 0.1 1/1 1
INACTIVE INGREDIENTS: Water; Phenoxyethanol; Glycerin; Sodium benzoate; Polysorbate 20; EDETATE DISODIUM ANHYDROUS; CITRIC ACID MONOHYDRATE; .ALPHA.-TOCOPHEROL ACETATE

ACTIVE INGREDIENT

Benzalkonium Chloride 0.1%

INACTIVE INGREDIENTS

Water (Aqua), Phenoxyethanol, Glycerin, Sodium benzoate, Polysorbate 20, Disodium EDTA, Citric Acid, Tocopheryl Acetate

PURPOSE

Antiseptic

handwash

WARNINGS

For external use only

Do not use
■ If you are allergic to any of the ingredients

When using this product
■ Do not get into eyes. If contact occurs, rinse thoroughly with water

Stop use and ask a doctor if
■ Irritation or rash develops and continues for more than 72 hours

Keep out of reach of children
■ Unless under adult supervision
■ If swallowed, get medical help or contact a Poison Control Center right away

KEEP OUT OF REACH OF CHILDREN

■ Unless under adult supervision
■ If swallowed, get medical help or contact a Poison Control Center right away

Uses

■ For hand washing to decrease bacteria on the skin

Directions

■ Use entire wipe to thoroughly wipe hands, fingers, and wrists
■ To sanitize, use multiple wipes
■ Discard after single use
■ Keep label closed to prevent moisture loss

Other information

■ Read the directions and warnings before use
■ Avoid freezing and excessive heat

Questions or Comments?

■ E-mail: cs@dkcos.com
■ Call 1-212-484-2621